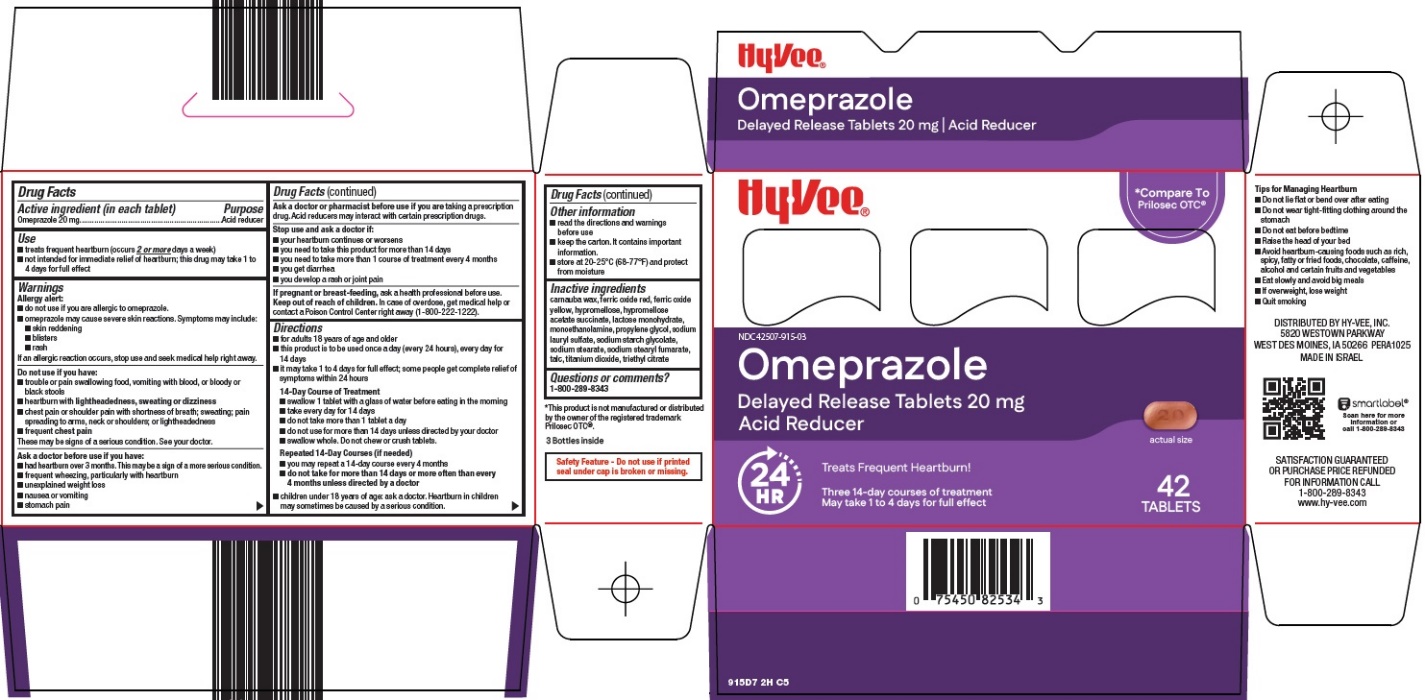 DRUG LABEL: omeprazole
NDC: 42507-915 | Form: TABLET, DELAYED RELEASE
Manufacturer: HyVee Inc
Category: otc | Type: HUMAN OTC DRUG LABEL
Date: 20260204

ACTIVE INGREDIENTS: OMEPRAZOLE 20 mg/1 1
INACTIVE INGREDIENTS: CARNAUBA WAX; FERRIC OXIDE RED; FERRIC OXIDE YELLOW; HYPROMELLOSE, UNSPECIFIED; HYPROMELLOSE ACETATE SUCCINATE 12070923 (3 MPA.S); LACTOSE MONOHYDRATE; MONOETHANOLAMINE; PROPYLENE GLYCOL; SODIUM LAURYL SULFATE; SODIUM STARCH GLYCOLATE TYPE A; SODIUM STEARATE; SODIUM STEARYL FUMARATE; TALC; TITANIUM DIOXIDE; TRIETHYL CITRATE

Hy-Vee, Inc. Omeprazole Drug Facts

Active ingredient (in each tablet)

Omeprazole 20 mg

Purpose

Acid reducer

Use

- treats frequent heartburn (occurs 2 or more days a week)
- not intended for immediate relief of heartburn; this drug may take 1 to 4 days for full effect

Warnings

Allergy alert:

- do not use if you are allergic to omeprazole.
- omeprazole may cause severe skin reactions. Symptoms may include:
  - skin reddening
  - blisters
  - rash

If an allergic reaction occurs, stop use and seek medical help right away.

Do not use

if you have:

- trouble or pain swallowing food, vomiting with blood, or bloody or black stools
- heartburn with lightheadedness, sweating or dizziness
- chest pain or shoulder pain with shortness of breath; sweating; pain spreading to arms, neck or shoulders; or lightheadedness
- frequent chest pain
  These may be signs of a serious condition. See your doctor.

Ask a doctor before use if you have:

- had heartburn over 3 months. This may be a sign of a more serious condition.
- frequent wheezing, particularly with heartburn
- unexplained weight loss
- nausea or vomiting
- stomach pain

Ask a doctor or pharmacist before use if you are

taking a prescription drug. Acid reducers may interact with certain prescription drugs.

Stop use and ask a doctor if:

- your heartburn continues or worsens
- you need to take this product for more than 14 days
- you need to take more than 1 course of treatment every 4 months
- you get diarrhea
- you develop a rash or joint pain

If pregnant or breast-feeding,

ask a health professional before use.

Keep out of reach of children.

In case of overdose, get medical help or contact a Poison Control Center right away (1-800-222-1222).

Directions

- for adults 18 years of age and older
- this product is to be used once a day (every 24 hours), every day for 14 days
- it may take 1 to 4 days for full effect; some people get complete relief of symptoms within 24 hours
  14-Day Course of Treatment
- swallow 1 tablet with a glass of water before eating in the morning
- take every day for 14 days
- do not take more than 1 tablet a day
- do not use for more than 14 days unless directed by your doctor
- swallow whole. Do not chew or crush tablets
  Repeated 14-Day Courses (if needed)
- you may repeat a 14-day course every 4 months
- do not take for more than 14 days or more often than every 4 months unless directed by a doctor
- children under 18 years of age: ask a doctor. Heartburn in children may sometimes be caused by a serious condition.

Other information

- read the directions and warnings before use
- keep the carton. It contains important information.
- store at 20-25°C (68-77°F) and protect from moisture

Inactive ingredients

carnauba wax, ferric oxide red, ferric oxide yellow, hypromellose, hypromellose acetate succinate, lactose monohydrate, monoethanolamine, propylene glycol, sodium lauryl sulfate, sodium starch glycolate, sodium stearate, sodium stearyl fumarate, talc, titanium dioxide, triethyl citrate

Questions or comments?

1-800-289-8343

Principal Display Panel

Hy•Vee®

Compare To Prilosec OTC®

Omeprazole

Delayed Release Tablets 20 mg

Acid Reducer

actual size

24 HR

Treats Frequent Heartburn!

Three 14-day courses of treatment

May take 1 to 4 days for full effect

42 TABLETS